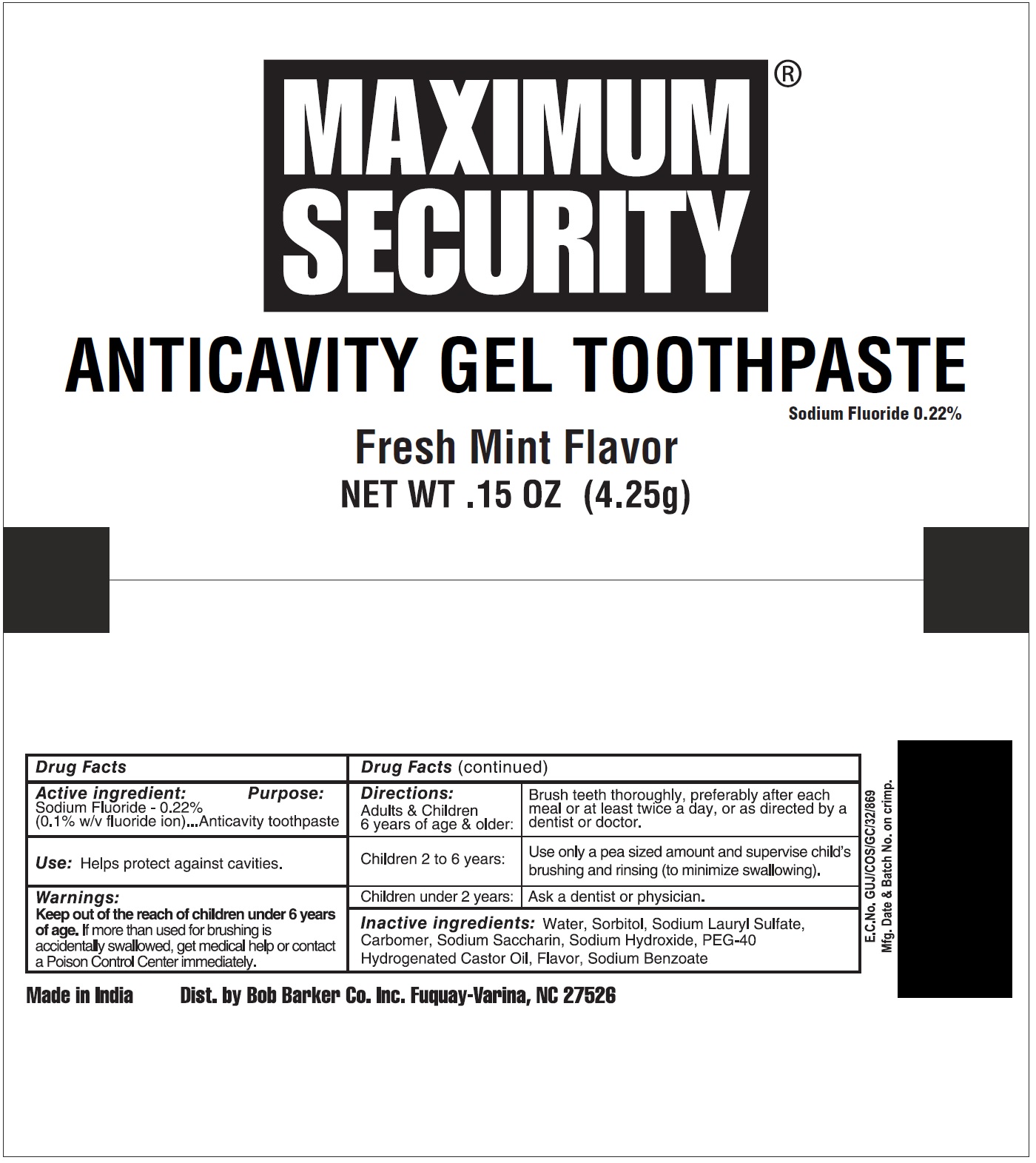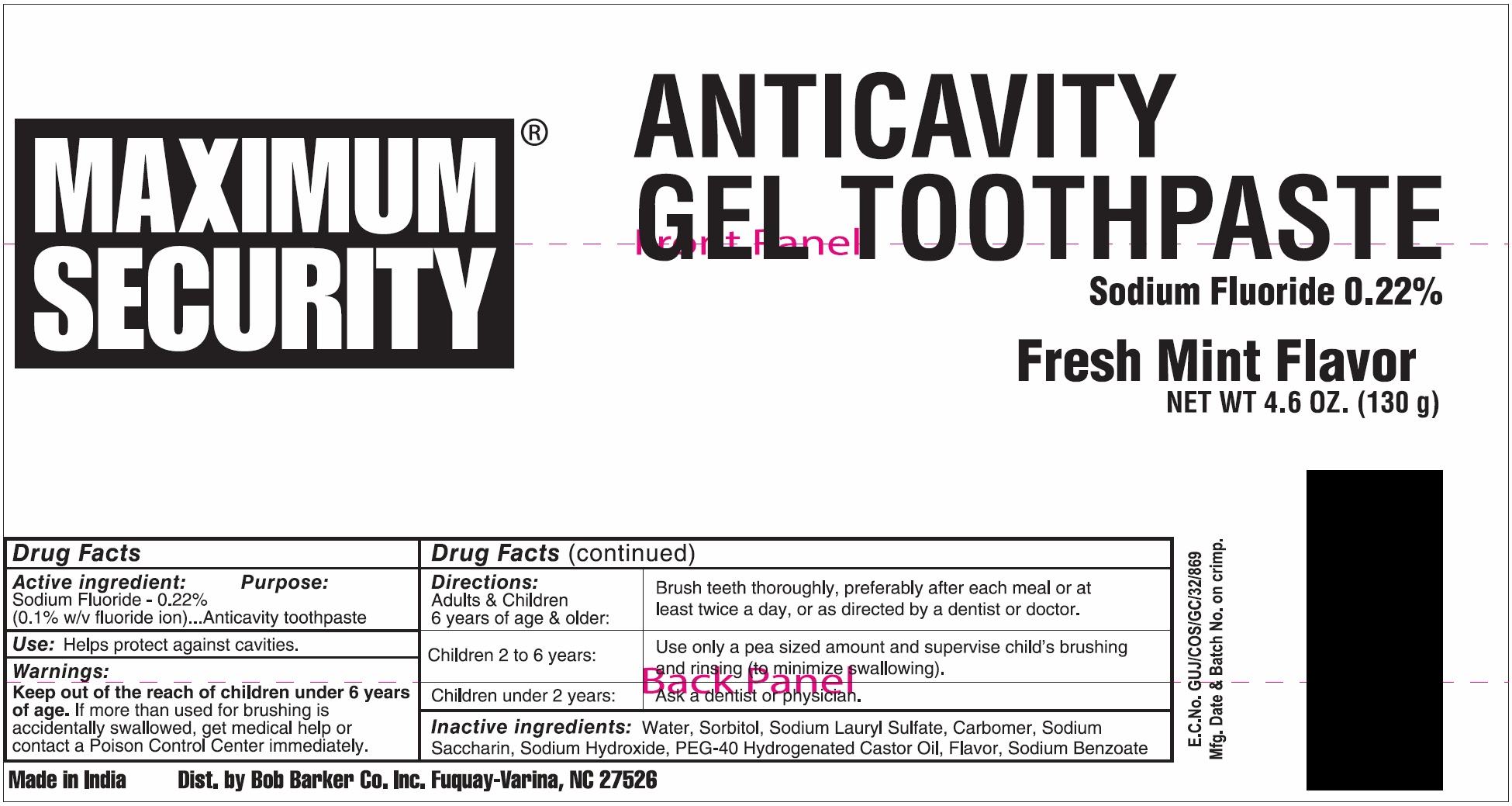 DRUG LABEL: MAXIMUM SECURITY ANTICAVITY
NDC: 53247-200 | Form: GEL
Manufacturer: Bob Barker Company, Inc.
Category: otc | Type: HUMAN OTC DRUG LABEL
Date: 20200131

ACTIVE INGREDIENTS: SODIUM FLUORIDE 2.2 mg/1 g
INACTIVE INGREDIENTS: WATER; SORBITOL; SODIUM LAURYL SULFATE; CARBOMER HOMOPOLYMER, UNSPECIFIED TYPE; SACCHARIN SODIUM; SODIUM HYDROXIDE; POLYOXYL 40 HYDROGENATED CASTOR OIL; SODIUM BENZOATE; METHYL SALICYLATE

MAXIMUM SECURITY ANTICAVITY TOOTHPASTE

Active ingredient:

Sodium Fluoride - 0.22% (0.1% w/ fluoride ion)

Purpose:

Anticavity toothpaste

Use:

Helps protect against cavities.

Warnings:

Keep out of the reach of children under 6 years of age.

If more than used for brushing is accidentally swallowed, get medical help or contact a Poison Control Center immediately.

Directions:

Adults & Children 6 years of age & older: | Brush teeth thoroughly, preferably after each meal or at least twice a day, or as directed by a dentist or doctor.
Children 2 to 6 years: | Use only a pea sized amount and supervise child's brushing and rinsing (to minimize swallowing).
Children under 2 years: | Ask a dentist or physician.

Inactive ingredients:

Water, Sorbitol, Sodium Lauryl Sulfate, Carbomer, Sodium Saccharin, Sodium Hydroxide, PEG-40 Hydrogenated Castor Oil, Flavor, Sodium Benzoate